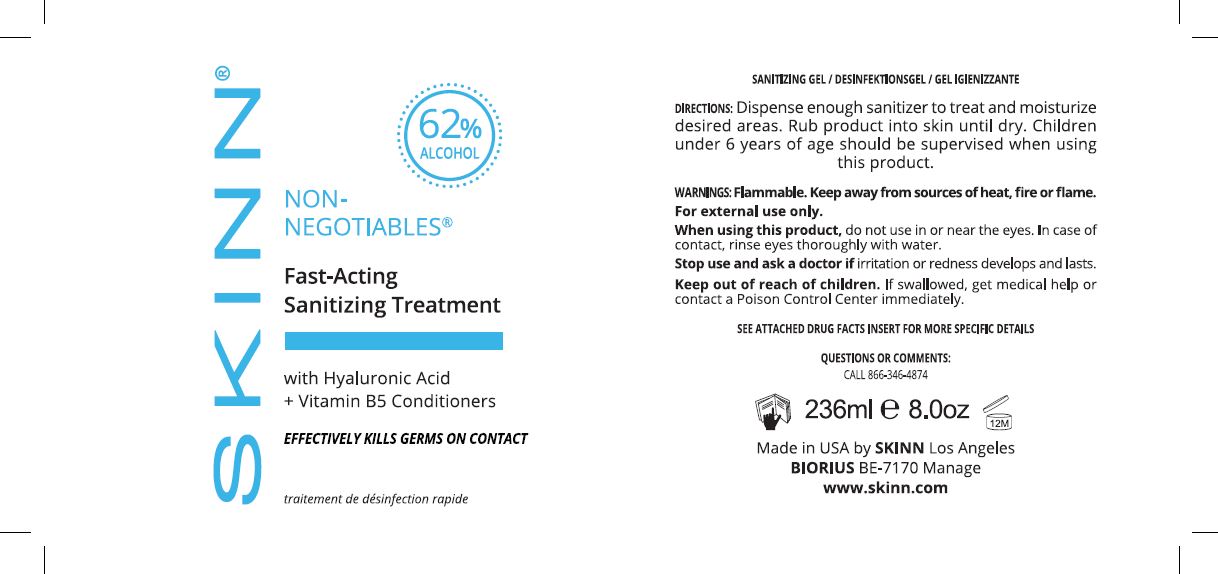 DRUG LABEL: Non-Negotiables Fast-Acting Sanitizing
NDC: 76286-668 | Form: GEL
Manufacturer: SKINN COSMETICS, LLC
Category: otc | Type: HUMAN OTC DRUG LABEL
Date: 20201006

ACTIVE INGREDIENTS: ALCOHOL 62 mL/100 mL
INACTIVE INGREDIENTS: AMINOMETHYLPROPANOL 0.25 g/100 mL; HYALURONIC ACID 7.5 mL/100 mL; CARBOMER 980 5 g/100 mL; METHYL GLUCETH-20 0.5 g/100 mL; WATER; ALOE VERA LEAF 0.001 g/100 mL; PANTHENOL 0.5 g/100 mL

SKINN Non-Negotiables Fast-Acting Sanitizing

STATEMENT OF IDENTITY

Hand Sanitizer

ACTIVE INGREDIENT

Ethyl Alcohol, 62% v/v

PURPOSE

Antiseptic

Uses

Sanitizer to reduce bacteria on the skin that could cause disease

Recommended for repeated use

WARNINGS

Flammable. Keep away from sources of heat, fire or flame.
For external use only.
When using this product, do not use in or near the eyes. In case of contact, rinse eyes thoroughly with water.
Stop use and ask a doctor if irritation or redness develops and lasts.
Keep out of reach of children. If swallowed, get medical help or contact a Poison Control Center immediately.

When using this product, do not use in or near the eyes. In case of contact, rinse eyes thoroughly with water.

Stop use and ask a doctor if irritation or redness develops and lasts.

Keep out of reach of children. If swallowed, get medical help or contact a Poison Control Center immediately.

Directions

Dispense enough sanitizer to cover desired areas

Rub product into skin until dry

Children under 6 years of age should be supervised when using this product

INACTIVE INGREDIENT

Water, Hyaluronic Acid, Aloe Barbadensis Leaf Juice, Panthenol, Aminomethyl Propanol, Carbomer, Methyl Gluceth-20, Fragrance

STORAGE AND HANDLING

Store at a temperature below 110ºF (43ºC)

May discolor certain fabrics or surfaces